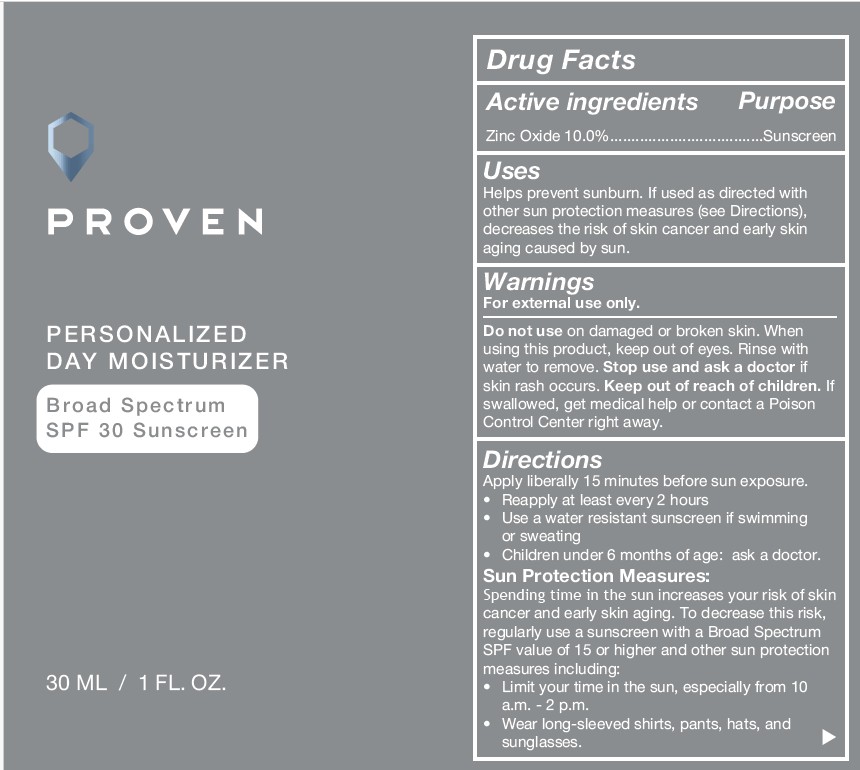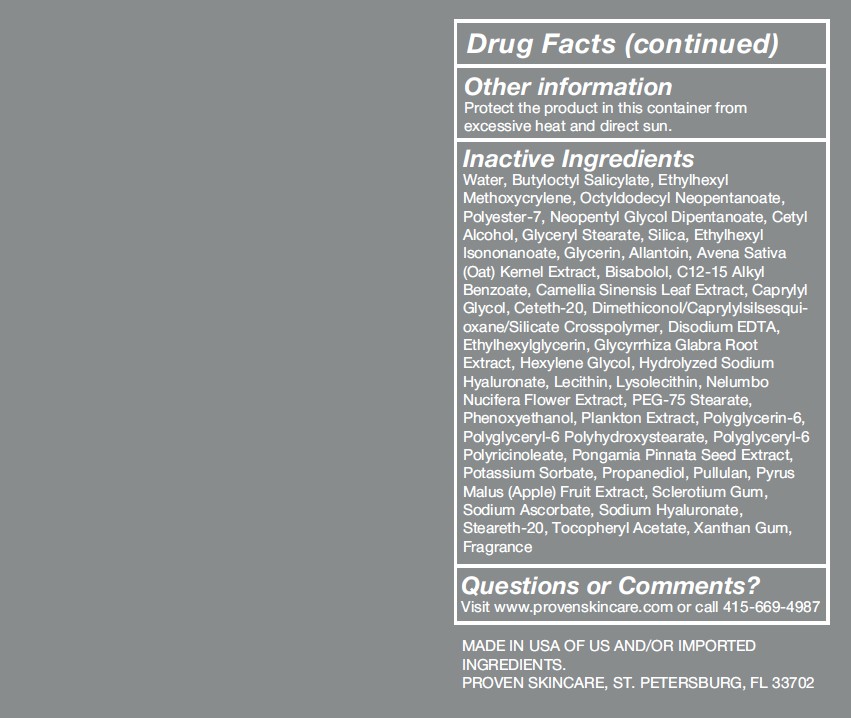 DRUG LABEL: Personalized Moisturizer SPF 30
NDC: 73572-012 | Form: LOTION
Manufacturer: Proven Skincare
Category: otc | Type: HUMAN OTC DRUG LABEL
Date: 20251208

ACTIVE INGREDIENTS: ZINC OXIDE 10 g/100 mL
INACTIVE INGREDIENTS: ALLANTOIN; OAT STRAW; BISABOLOL; BUTYLOCTYL SALICYLATE; C12-15 ALKYL BENZOATE; CAMELLIA SINENSIS LEAF; CAPRYLYL GLYCOL; CETETH-20; CETYL ALCOHOL; EDETATE DISODIUM; ETHYLHEXYL ISONONANOATE; ETHYLHEXYL METHOXYCRYLENE; ETHYLHEXYLGLYCERIN; GLYCERIN; GLYCERYL STEARATE; GLYCYRRHIZA GLABRA (LICORICE) ROOT; HEXYLENE GLYCOL; HYALURONATE SODIUM; SOYBEAN LECITHIN; LYSOPHOSPHATIDYLCHOLINE, SOYBEAN; NELUMBO NUCIFERA FLOWER; NEOPENTYL GLYCOL DIHEPTANOATE; OCTYLDODECYL NEOPENTANOATE; PEG-75 STEARATE; PHENOXYETHANOL; POLYESTER-7; POLYGLYCERIN-6; POLYGLYCERYL-6 POLYRICINOLEATE; PONGAMIA PINNATA ROOT; POTASSIUM SORBATE; PROPANEDIOL; PULLULAN; APPLE; SCLEROTIUM GUM; SILICA; SODIUM ASCORBATE

Proven Personalized Day Moisturizer SPF 30 Lotion

Active ingredients Purpose

Zinc Oxide 10.0%....................Sunscreen

Uses

Helps prevent sunburn. If used as directed with
other sun protection measures (see Directions),
decreases the risk of skin cancer and early skin
aging caused by sun.

Directions

Apply liberally 15 minutes before sun exposure.
• Reapply at least every 2 hours
• Use a water resistant sunscreen if swimming
or sweating
• Children under 6 months of age: ask a doctor.
Sun Protection Measures:
Spending time in the sun increases your risk of skin
cancer and early skin aging. To decrease this risk,
regularly use a sunscreen with a Broad Spectrum
SPF value of 15 or higher and other sun protection
measures including:
• Limit your time in the sun, especially from 10
a.m. - 2 p.m.
• Wear long-sleeved shirts, pants, hats, and
sunglasses.

Warnings For external use only.

Do not use on damaged or broken skin. When
using this product, keep out of eyes. Rinse with
water to remove. Stop use and ask a doctor if
skin rash occurs.

Keep out of reach of children.

If
swallowed, get medical help or contact a Poison
Control Center right away.

Inactive Ingredients

Water, Butyloctyl Salicylate, Ethylhexyl
Methoxycrylene, Octyldodecyl Neopentanoate,
Polyester-7, Neopentyl Glycol Dipentanoate, Cetyl
Alcohol, Glyceryl Stearate, Silica, Ethylhexyl
Isononanoate, Glycerin, Allantoin, Avena Sativa
(Oat) Kernel Extract, Bisabolol, C12-15 Alkyl
Benzoate, Camellia Sinensis Leaf Extract, Caprylyl
Glycol, Ceteth-20, Dimethiconol/Caprylylsilsesquioxane/
Silicate Crosspolymer, Disodium EDTA,
Ethylhexylglycerin, Glycyrrhiza Glabra Root
Extract, Hexylene Glycol, Hydrolyzed Sodium
Hyaluronate, Lecithin, Lysolecithin, Nelumbo
Nucifera Flower Extract, PEG-75 Stearate,
Phenoxyethanol, Plankton Extract, Polyglycerin-6,
Polyglyceryl-6 Polyhydroxystearate, Polyglyceryl-6
Polyricinoleate, Pongamia Pinnata Seed Extract,
Potassium Sorbate, Propanediol, Pullulan, Pyrus
Malus (Apple) Fruit Extract, Sclerotium Gum,
Sodium Ascorbate, Sodium Hyaluronate,
Steareth-20, Tocopheryl Acetate, Xanthan Gum,
Fragrance